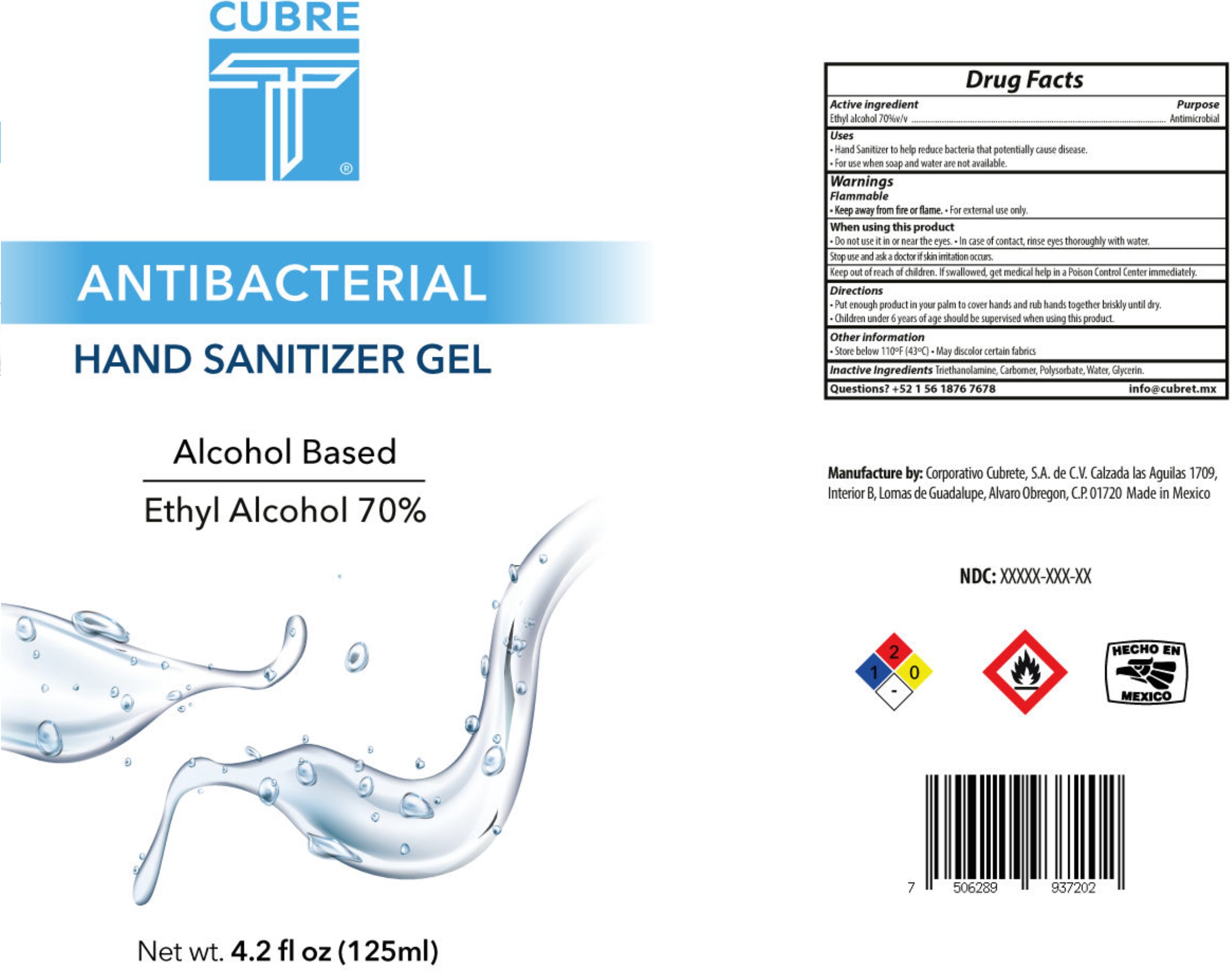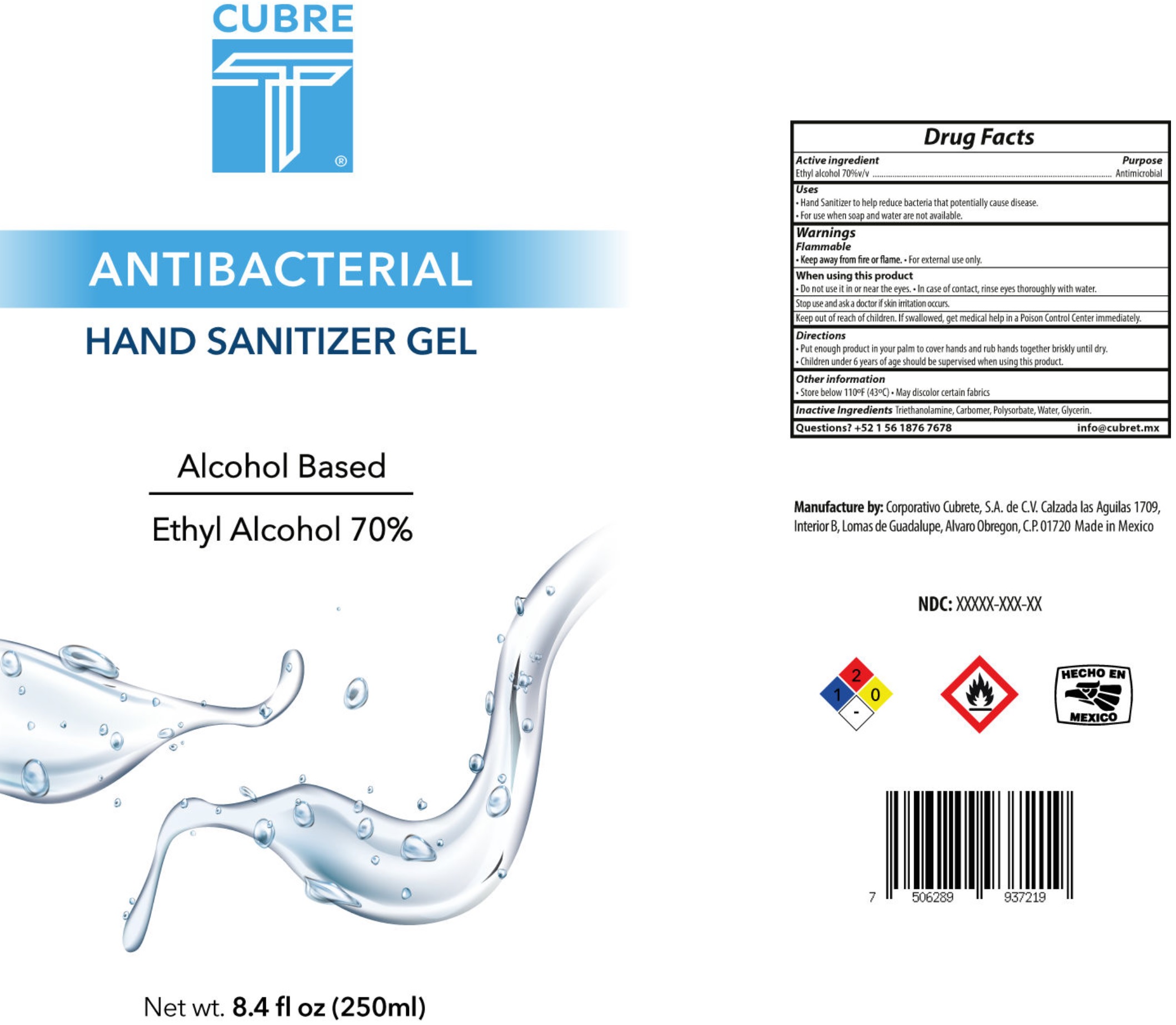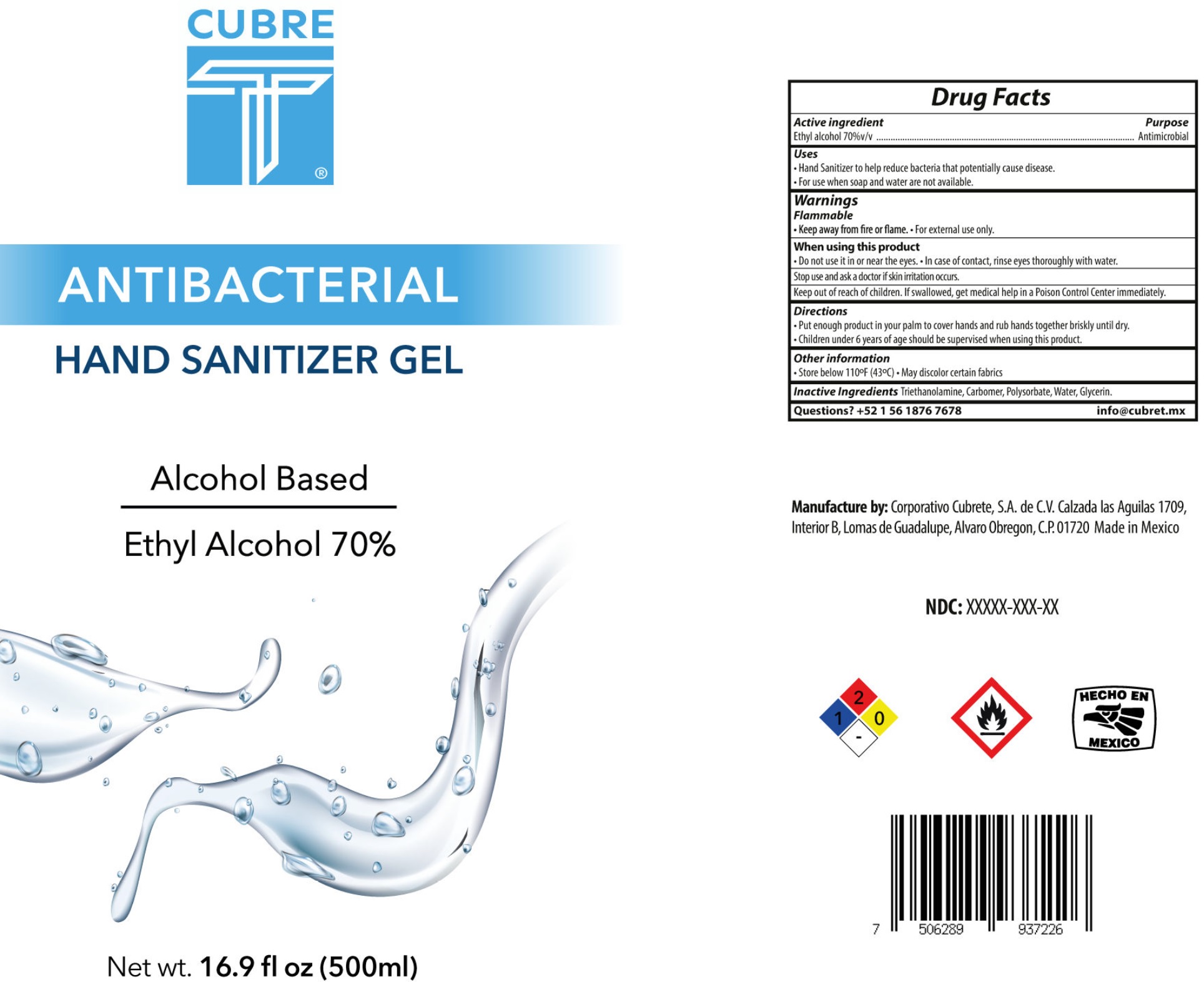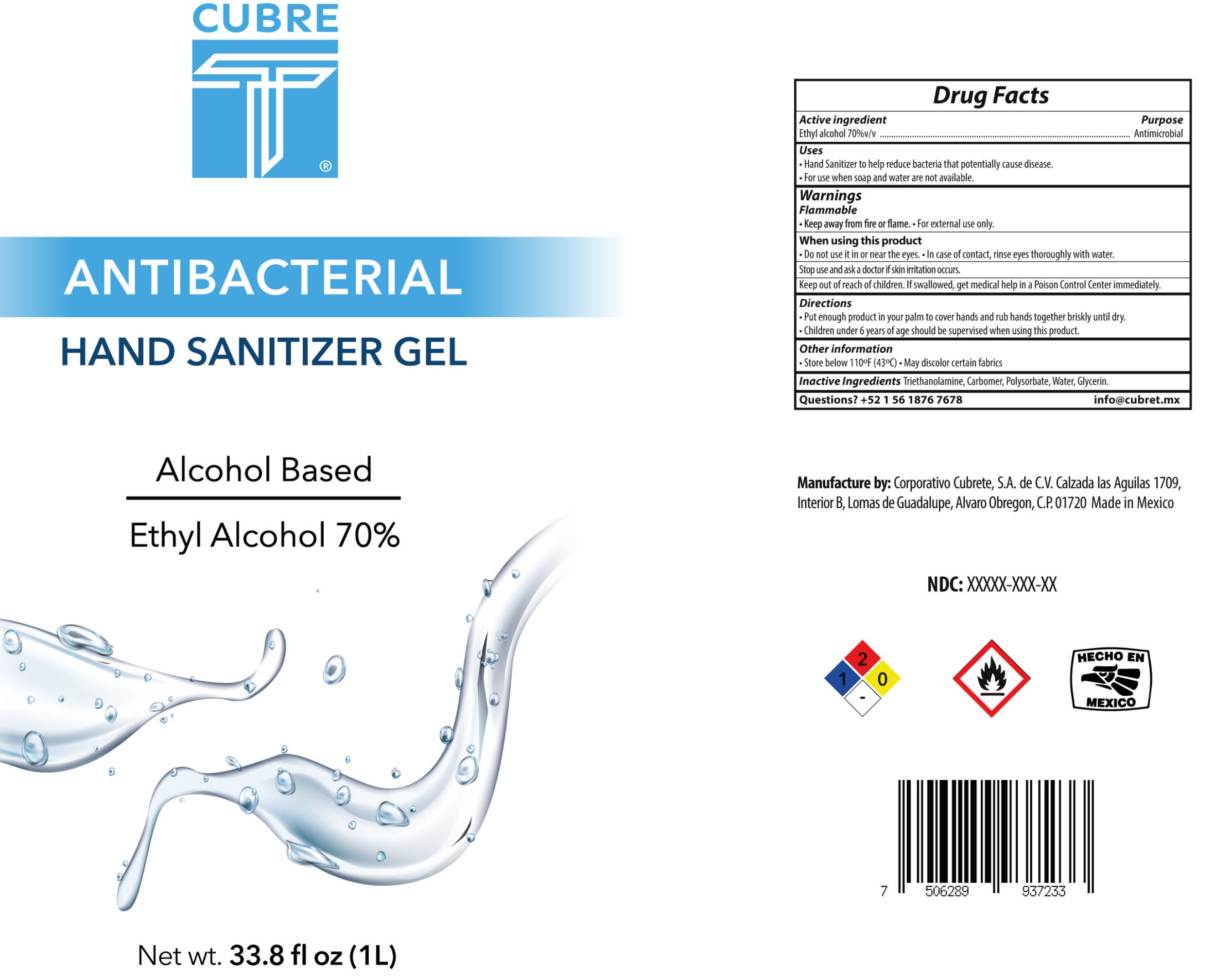 DRUG LABEL: Cubre T Hand Sanitizer
NDC: 79410-000 | Form: GEL
Manufacturer: Corporativo Cubrete, S.A. de C.V.
Category: otc | Type: HUMAN OTC DRUG LABEL
Date: 20220104

ACTIVE INGREDIENTS: ALCOHOL 0.7 mL/1 mL
INACTIVE INGREDIENTS: TROLAMINE; CARBOMER HOMOPOLYMER, UNSPECIFIED TYPE; WATER; GLYCERIN

Cubre T Hand Sanitizer Gel

Active ingredient

Ethyl alcohol 70%v/v

Purpose

Antimicrobial

Uses

- Hand Sanitizer to help reduce bacteria that potentially cause disease.
- For use when soap and water are not available.

Warnings

Flammable

- Keep away from fire or flame.
- For external use only.

When using this product

- Do not use it in or near the eyes.
- In case of contact, rinse eyes thoroughly with water.

Stop use and ask a doctor

if skin irritation occurs.

Keep out of reach of children.

If swallowed, get medical help in a Poison Control Center immediately.

Directions

- Put enough product in your palm to cover hands and rub hands together briskly until dry.
- Children under 6 years of age should be supervised when using this product.

Other information

- Store below 110°F (43°C)
- May discolor certain fabrics

Inactive Ingredients

Triethannolamine, Carbomer, Polysorbate, Water, Glycerin.

Questions?

+52 1 56 1876 7678 info@cubret.mx